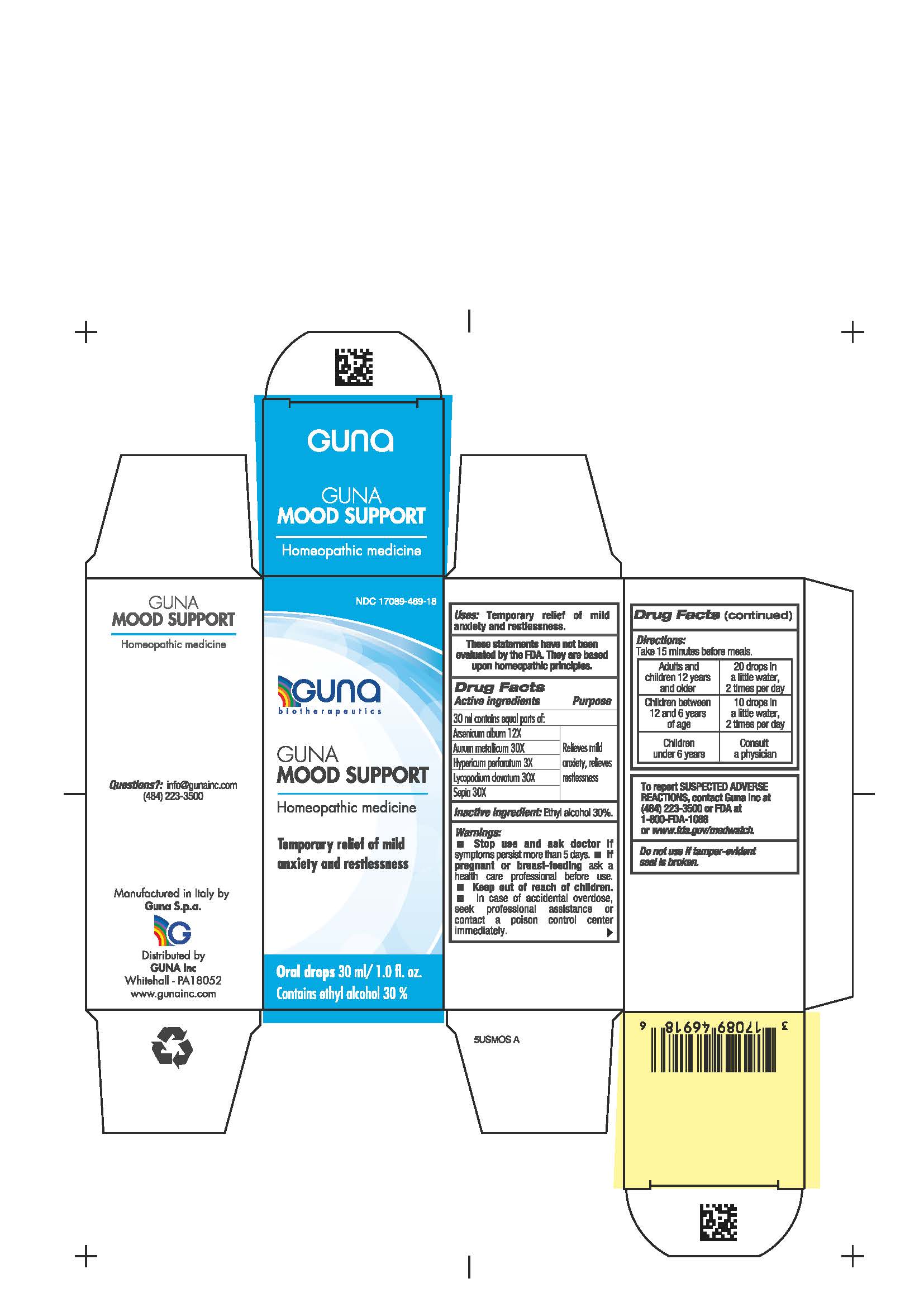 DRUG LABEL: GUNA MOOD SUPPORT
NDC: 17089-469 | Form: SOLUTION/ DROPS
Manufacturer: Guna spa
Category: homeopathic | Type: HUMAN OTC DRUG LABEL
Date: 20210117

ACTIVE INGREDIENTS: SEPIA OFFICINALIS JUICE 30 [hp_X]/30 mL; ARSENIC TRIOXIDE 12 [hp_X]/30 mL; HYPERICUM PERFORATUM 3 [hp_X]/30 mL; GOLD 30 [hp_X]/30 mL; LYCOPODIUM CLAVATUM SPORE 30 [hp_X]/30 mL
INACTIVE INGREDIENTS: ALCOHOL 9 mL/30 mL

GUNA MOOD SUPPORT

USES

- Temporary relief of mild anxiety and restlessness

ACTIVE INGREDIENTS/PURPOSE

ARSENICUM ALBUM 12X RELIEVES MILD ANXIETY, RELIEVES RESTLESSNESS

AURUM METALLICUM 30X RELIEVES MILD ANXIETY, RELIEVES RESTLESSNESS

HYPERICUM PERFORATUM 3X RELIEVES MILD ANXIETY, RELIEVES RESTLESSNESS

LYCOPODIUM CLAVATUM 30X RELIEVES MILD ANXIETY, RELIEVES RESTLESSNESS

SEPIA OFFICINALIS 30X RELIEVES MILD ANXIETY, RELIEVES RESTLESSNESS

Inactive ingredient: Ethyl alcohol 30%.

QUESTIONS

info@gunainc.com
Tel. (484) 223-3500

WARNINGS

Keep out of reach of children.

INDICATIONS AND USAGE

Take 15 minutes before meals.

DIRECTIONS

Take 15 minutes before meals.

Adults and children twelve years and older: 20 drops in a little water, 2 times per day

Children between 12 years and 6 years of age: 10 drops in a little water, 2 times per day

Children under 6 years: consult a physician

PREGNANCY

If pregnant or breast-feeding ask a health care profesisonal before use.

WARNINGS

- Stop use and ask doctor if symptoms worsen or persist more than 5 days.
- If pregnant or breast-feeding ask a health care professional before use.
- Keep out of reach of children.
- In case of accidental overdose, seek professional assistance or contact a poison control center immediately
- Contains ethyl alcohol 30%